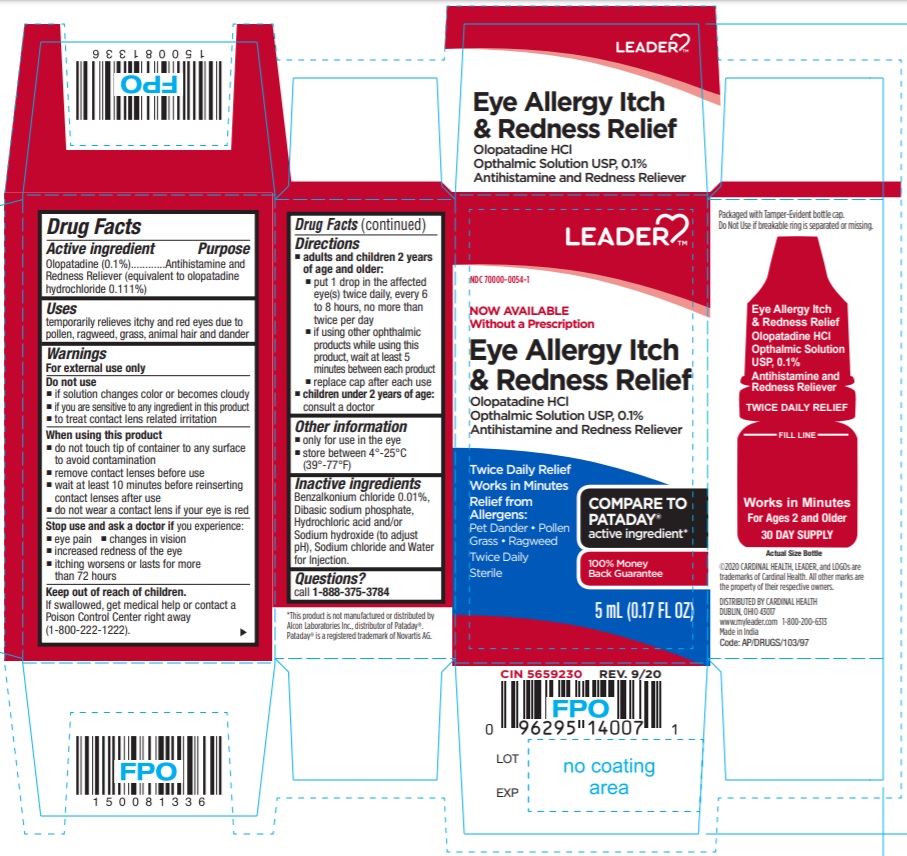 DRUG LABEL: Eye Allergy Itch and Redness Relief
NDC: 70000-0054 | Form: SOLUTION/ DROPS
Manufacturer: CARDINAL HEALTH 110, LLC. DBA LEADER
Category: otc | Type: Human OTC Drug Label
Date: 20251210

ACTIVE INGREDIENTS: OLOPATADINE HYDROCHLORIDE 1 mg/1 mL
INACTIVE INGREDIENTS: BENZALKONIUM CHLORIDE; SODIUM PHOSPHATE, DIBASIC; HYDROCHLORIC ACID; SODIUM CHLORIDE; SODIUM HYDROXIDE; WATER

ACTIVE INGREDIENT

Olopatadine (0.1%) (equivalent to olopatadine hydrochloride 0.111%)

PURPOSE

Antihistamine and redness reliever

USES

temporarily relieves itchy and red eyes due to pollen, ragweed, grass, animal hair and dander

WARNINGS

For external use only

DO NOT USE

• if solution changes color or becomes cloudy
• if you are sensitive to any ingredient in this product
• to treat contact lens related irritation

WHEN USING THIS PRODUCT

- do not touch tip of container to any surface to avoid contamination
- remove contact lenses before use
- wait at least 10 minutes before reinserting contact lenses after use
- do not wear a contact lens if your eye is red

STOP USE AND ASK DOCTOR IF

you experience:

- eye pain
- changes in vision
- increased redness of the eye
- itching worsens or lasts for more than 72 hours

KEEP OUT OF REACH OF CHILDREN

If swallowed, get medical help or contact a Poison Control Center right away.

DIRECTIONS

• adults and children 2 years of age and older:
• put 1 drop in the affected eye(s) twice daily, every 6 to 8 hours, no more than twice per day
• if using other ophthalmic products while using this product, wait at least 5 minutes between each product
• replace cap after each use
• children under 2 years of age: consult a doctor

OTHER INFORMATION

• only for use in the eye
• store between 4° to 25°C (39° to 77°F)

INACTIVE INGREDIENTS

Benzalkonium chloride 0.01%, Dibasic sodium phosphate, Hydrochloric acid and /or Sodium hydroxide (to adjust pH), Sodium chloride and Water for Injection.

QUESTIONS?

Call 1-888-375-3784

PRINCIPAL DISPLAY PANEL

Olopatadine Hydrochloride Ophthalmic Solution USP, 0.1%

NOW AVAILABLE Without a Prescription

Eye Allergy Itch & Redness Relief

Olopatadine HCl

Ophthalmic solution USP, 0.1%

Antihistamine and Redness Reliever

Twice Daily Relief

Works in Minutes

Relief from Allergens:

• Pet Dander • Pollen • Grass • Ragweed

Twice Daily

Sterile

5 mL (0.17 FL OZ)

For Ages 2 and Older

30 DAY SUPPLY

Packaged with Tamper-Evident bottle cap. Do Not Use if breakable ring is separated or missing.

COMPARE TO PATADAY® active ingredient*

©2020 CARDINAL HEALTH, LEADER, and LOGOs are trademarks of Cardinal Health. All other marks are the property of their respective owners.

DISTRIBUTED BY CARDINAL HEALTH

DUBLIN, OHIO 43017

www.myleader.com 1-800-200-6313

Made in India

Code: AP/DRUGS/103/97

CIN 5659230 REV. 9/20

*This product is not manufactured or distributed by Alcon Laboratories Inc., distributor of Pataday®. Pataday® is a registered trademark of Novartis AG.